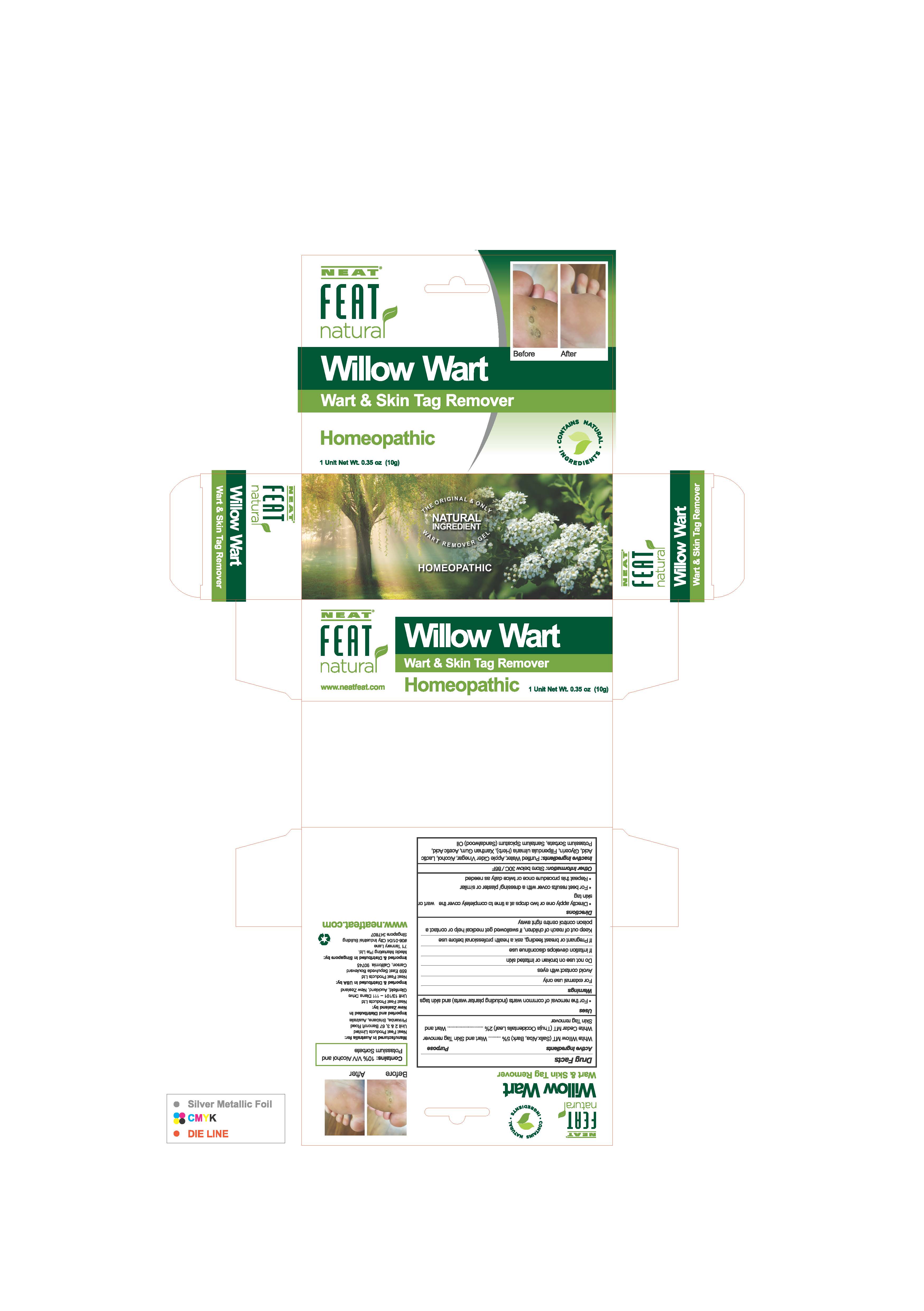 DRUG LABEL: Willow Wart
NDC: 50017-032 | Form: CREAM
Manufacturer: Neat Feat Products Limited
Category: homeopathic | Type: HUMAN OTC DRUG LABEL
Date: 20250108

ACTIVE INGREDIENTS: SALIX ALBA BARK 0.5 g/10 g; THUJA OCCIDENTALIS LEAF 0.2 g/10 g
INACTIVE INGREDIENTS: APPLE CIDER VINEGAR; LACTIC ACID; WATER; FILIPENDULA ULMARIA WHOLE; SANTALUM SPICATUM OIL; GLYCERIN; ALCOHOL; XANTHAN GUM; ACETIC ACID; POTASSIUM SORBATE

Willow Wart

ACTIVE INGREDIENT

White Willow (Salix Alba bark)

White Cedar (Thuja Occidentalis leaf)

PURPOSE

White Willow (Salix Alba stem and bark)..........Wart and Skin tag remover

White Cedar (Thuja Occidentalis leaf)..............Wart and Skin tag remover

INDICATIONS AND USAGE

For the removal of common warts (including plantar warts) and skin tags

WARNINGS

For external use only

Avoid contact with eyes

Do not use on broken or irritated skin

If irritation develops discontinue use

If pregnant or breast feeding, ask a health professional before use

Keep out of reach of children. If swallowed get medical help or contact a poison control centre right away.

INACTIVE INGREDIENT

Purified Water, Apple Cider Vinegar, Alcohol, Lactic Acid, Filipendula Ulmaria Whole Plant, Glycerin, Acetic Acid, Potassium Sorbate, Santalum Spicatum (Sandalwood) Oil, Xanthan Gum

DOSAGE AND ADMINISTRATION

Directly apply one or two drops at a time to completely cover the wart or skin tag
For best results cover with a dressing/plaster or similar
Repeat this procedure once or twice daily as needed

OTHER SAFETY INFORMATION

Store below 30C/86F

Keep out of reach of children

Willow Wart Label 10g

50017-032-01